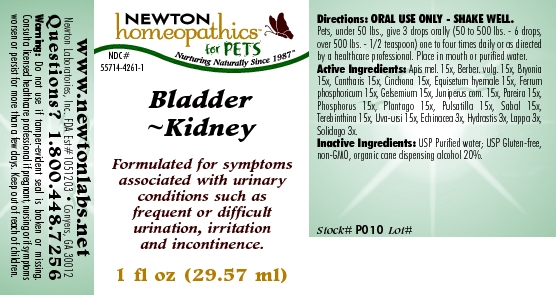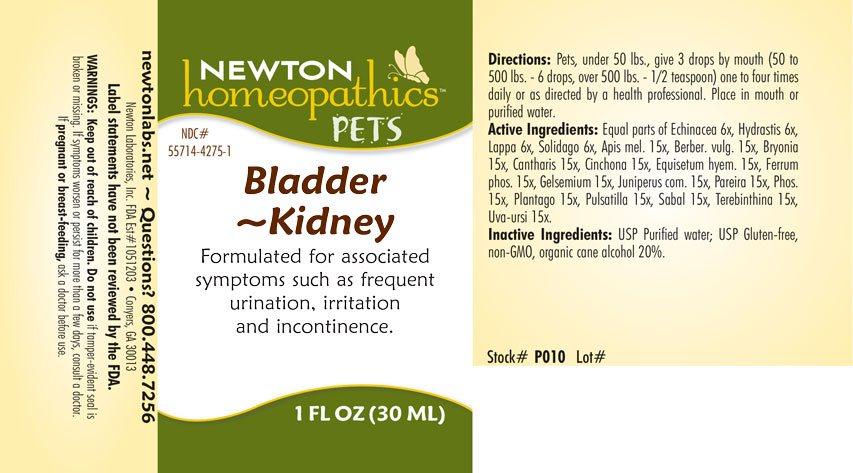 DRUG LABEL: BLADDER KIDNEY
NDC: 55714-4261 | Form: LIQUID
Manufacturer: Newton Laboratories, Inc.
Category: homeopathic | Type: OTC ANIMAL DRUG LABEL
Date: 20190114

ACTIVE INGREDIENTS: Apis Mellifera 15 [hp_X]/1 mL; Berberis Vulgaris Root Bark 15 [hp_X]/1 mL; Bryonia Alba Root 15 [hp_X]/1 mL; Lytta Vesicatoria 15 [hp_X]/1 mL; Cinchona Officinalis Bark 15 [hp_X]/1 mL; Equisetum Hyemale 15 [hp_X]/1 mL; Ferrosoferric Phosphate 15 [hp_X]/1 mL; Gelsemium Sempervirens Root 15 [hp_X]/1 mL; Juniper Berry 15 [hp_X]/1 mL; Chondrodendron Tomentosum Root 15 [hp_X]/1 mL; Phosphorus 15 [hp_X]/1 mL; Plantago Major 15 [hp_X]/1 mL; Pulsatilla Vulgaris 15 [hp_X]/1 mL; Saw Palmetto 15 [hp_X]/1 mL; Turpentine Oil 15 [hp_X]/1 mL; Arctostaphylos Uva-ursi Leaf 15 [hp_X]/1 mL; Echinacea, Unspecified 3 [hp_X]/1 mL; Goldenseal 3 [hp_X]/1 mL; Arctium Lappa Root 3 [hp_X]/1 mL; Solidago Virgaurea Flowering Top 3 [hp_X]/1 mL
INACTIVE INGREDIENTS: Alcohol

Bladder - Kidney

INDICATIONS & USAGE SECTION

Bladder Kidney Formulated for associated symptoms such as frequent urination, irritation and incontinence.

DOSAGE & ADMINISTRATION SECTION

Directions: Pets, under 50 lbs., give 3 drops by mouth (50 to 500 lbs. - 6 drops, over 500 lbs. - 1/2 teaspoon) one to four times daily or as directed by a health professional. Place in mouth or purified water.

OTC - ACTIVE INGREDIENT SECTION

Equal Parts of Echinacea 6x, Hydrastis 6x, Lappa 6x, Solidago 6x, Apis mel. 15x, Berber. vulg. 15x, Bryonia 15x, Cantharis 15x, Cinchona 15x, Equisetum hyem. 15x, Ferrum phos. 15x, Gelsemium 15x, Juniperus com. 15x, Pareira 15x, Phos. 15x, Plantago 15x, Pulsatilla 15x, Sabal 15x, Terebinthina 15x, Uva-ursi 15x.

OTC - PURPOSE SECTION

Formulated for associated symptoms such as frequent urination, irritation and incontinence.

INACTIVE INGREDIENT SECTION

Inactive Ingredients: USP Purified Water; USP Gluten-free, non-GMO, organic cane alcohol 20%.

QUESTIONS SECTION

Newton Laboratories, Inc. FDA Est # 1051203 - Conyers, GA 30013
newtonlabs.net Questions? 1.800.448.7256

WARNINGS SECTION

Warnings: Keep out of reach of children. Do not use if tamper-evident seal is broken or missing. If symptoms worsen or persist for more than a few days, consult a doctor. If pregnant or breast-feeding, ask a doctor before use.

OTC - PREGNANCY OR BREAST FEEDING SECTION

If pregnant or breast-feeding, ask a doctor before use.

OTC - KEEP OUT OF REACH OF CHILDREN SECTION

Keep out of reach of children.